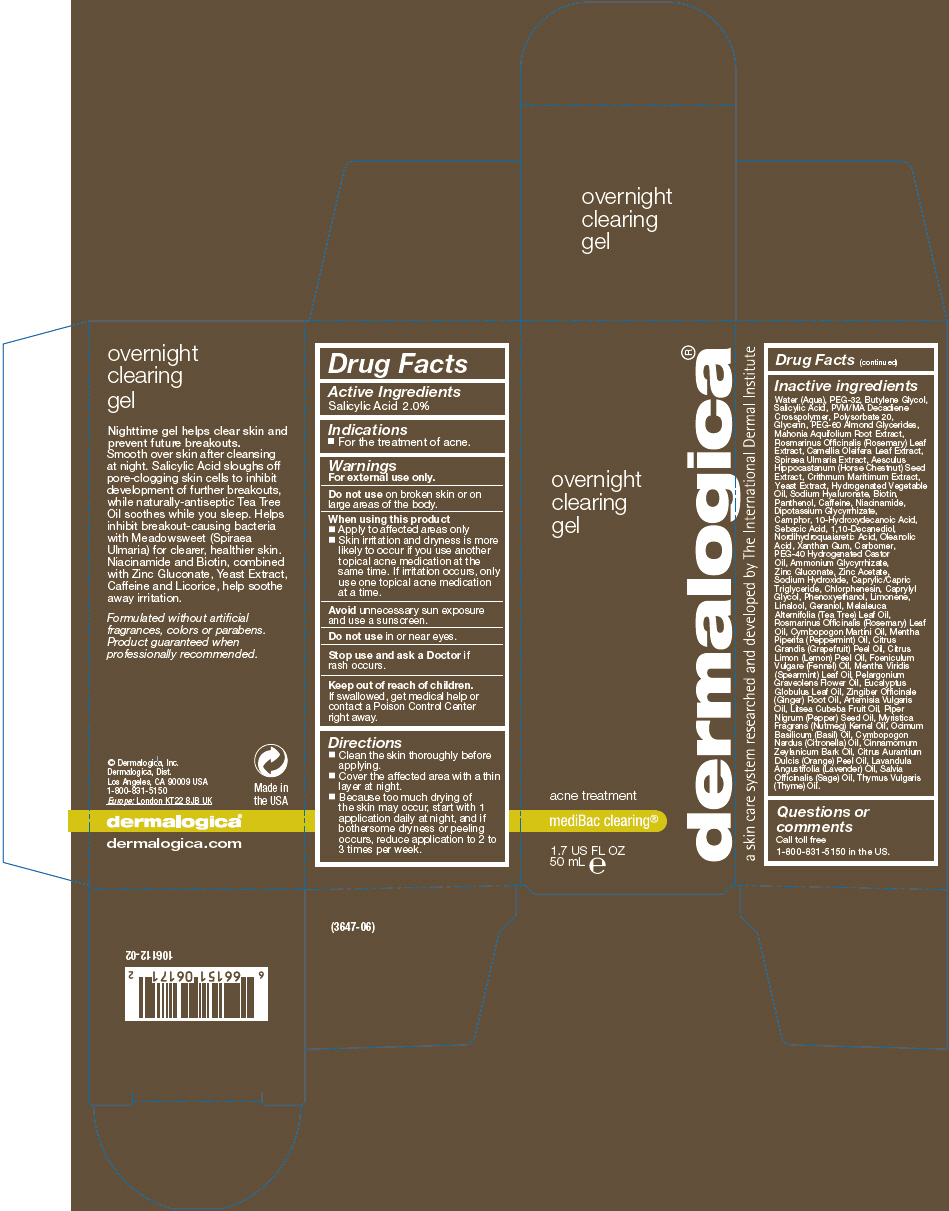 DRUG LABEL: Overnight Clearing
NDC: 68479-706 | Form: GEL
Manufacturer: Dermalogica, Inc.
Category: otc | Type: HUMAN OTC DRUG LABEL
Date: 20171204

ACTIVE INGREDIENTS: Salicylic Acid 20 mg/1 mL
INACTIVE INGREDIENTS: Water; Polyethylene Glycol 1500; Butylene Glycol; Polysorbate 20; Glycerin; PEG-60 Almond Glycerides; BERBERIS AQUIFOLIUM ROOT; Rosemary; Camellia Oleifera Leaf; Filipendula Ulmaria Root; Horse Chestnut; Crithmum Maritimum; Yeast, Unspecified; Hyaluronate Sodium; Biotin; Panthenol; Caffeine; Niacinamide; Glycyrrhizinate Dipotassium; Camphor (Synthetic); 10-Hydroxydecanoic Acid; Sebacic Acid; 1,10-Decanediol; Masoprocol; Oleanolic Acid; Xanthan Gum; Carbomer Homopolymer Type C (Allyl Pentaerythritol Crosslinked); Polyoxyl 40 Hydrogenated Castor Oil; Ammonium Glycyrrhizate; Zinc Gluconate; Zinc Acetate; Sodium Hydroxide; Medium-Chain Triglycerides; Chlorphenesin; Caprylyl Glycol; Phenoxyethanol; Tea Tree Oil; Rosemary Oil; Palmarosa Oil; Peppermint Oil; Citrus Maxima Fruit Rind Oil; Lemon Oil; Fennel Oil; Spearmint Oil; Pelargonium Graveolens Flower Oil; Eucalyptus Oil; Ginger Oil; Artemisia Vulgaris Top Oil; Litsea Oil; White Pepper Oil; Nutmeg Oil; Basil Oil; Citronella Oil; Cinnamon Bark Oil; Orange Oil; Lavender Oil; Sage Oil; Thyme Oil

Overnight Clearing Gel

Drug Facts

Active Ingredients

Salicylic Acid 2.0%

Indications

PURPOSE

- For the treatment of acne.

Warnings

For external use only.

Do not use on broken skin or on large areas of the body.

When using this product

- Apply to affected areas only
- Skin irritation and dryness is more likely to occur if you use another topical acne medication at the same time. If irritation occurs, only use one topical acne medication at a time.

Avoid unnecessary sun exposure and use a sunscreen.

Do not use in or near eyes.

Stop use and ask a Doctor if rash occurs.

Keep out of reach of children.

If swallowed, get medical help or contact a Poison Control Center right away.

Directions

- Clean the skin thoroughly before applying.
- Cover the affected area with a thin layer at night.
- Because too much drying of the skin may occur, start with 1 application daily at night, and if bothersome dryness or peeling occurs, reduce application to 2 to 3 times per week.

Inactive ingredients

Water (Aqua), PEG-32, Butylene Glycol, Salicylic Acid, PVM/MA Decadiene Crosspolymer, Polysorbate 20, Glycerin, PEG-60 Almond Glycerides, Mahonia Aquifolium Root Extract, Rosmarinus Officinalis (Rosemary) Leaf Extract, Camellia Oleifera Leaf Extract, Spiraea Ulmaria Extract, Aesculus Hippocastanum (Horse Chestnut) Seed Extract, Crithmum Maritimum Extract, Yeast Extract, Hydrogenated Vegetable Oil, Sodium Hyaluronate, Biotin, Panthenol, Caffeine, Niacinamide, Dipotassium Glycyrrhizate, Camphor, 10-Hydroxydecanoic Acid, Sebacic Acid, 1,10-Decanediol, Nordihydroquaiaretic Acid, Oleanolic Acid, Xanthan Gum, Carbomer, PEG-40 Hydrogenated Castor Oil, Ammonium Glycyrrhizate, Zinc Gluconate, Zinc Acetate, Sodium Hydroxide, Caprylic/Capric Triglyceride, Chlorphenesin, Caprylyl Glycol, Phenoxyethanol, Limonene, Linalool, Geraniol, Melaleuca Alternifolia (Tea Tree) Leaf Oil, Rosmarinus Officinalis (Rosemary) Leaf Oil, Cymbopogon Martini Oil, Mentha Piperita (Peppermint) Oil, Citrus Grandis (Grapefruit) Peel Oil, Citrus Limon (Lemon) Peel Oil, Foeniculum Vulgare (Fennel) Oil, Mentha Viridis (Spearmint) Leaf Oil, Pelargonium Graveolens Flower Oil, Eucalyptus Globulus Leaf Oil, Zingiber Officinale (Ginger) Root Oil, Artemisia Vulgaris Oil, Litsea Cubeba Fruit Oil, Piper Nigrum (Pepper) Seed Oil, Myristica Fragrans (Nutmeg) Kernel Oil, Ocimum Basilicum (Basil) Oil, Cymbopogon Nardus (Citronella) Oil, Cinnamomum Zeylanicum Bark Oil, Citrus Aurantium Dulcis (Orange) Peel Oil, Lavandula Angustifolia (Lavender) Oil, Salvia Officinalis (Sage) Oil, Thymus Vulgaris (Thyme) Oil.

Questions or comments

Call toll free 1-800-831-5150 in the US.

PRINCIPAL DISPLAY PANEL - 50 mL Bottle Carton

overnight
clearing
gel

acne treatment

mediBac clearing®

1.7 US FL OZ
50 mL e

dermalogica®